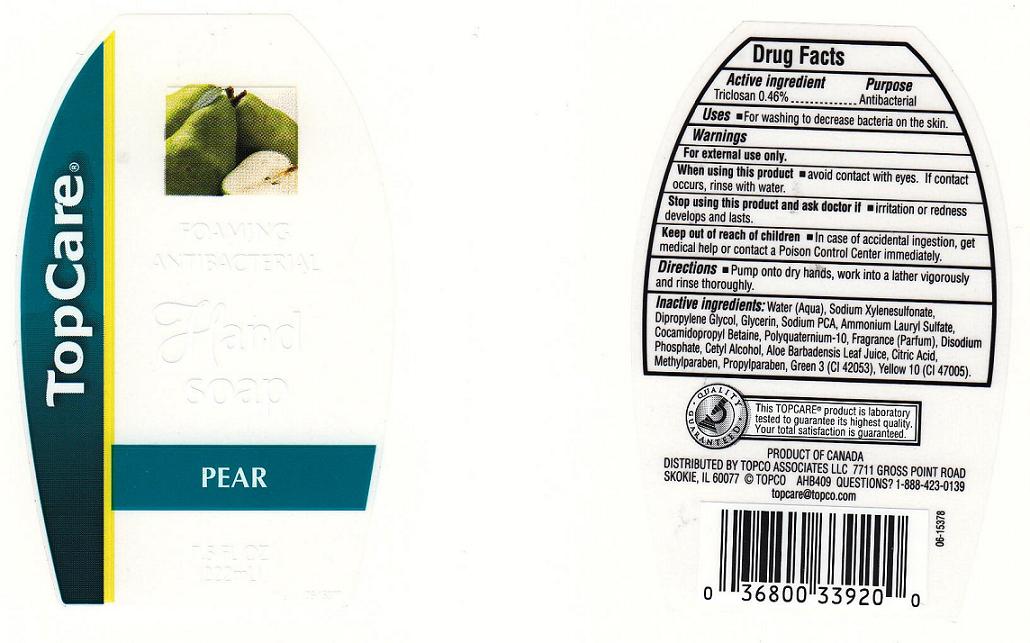 DRUG LABEL: Foaming Antibacterial 
NDC: 36800-163 | Form: SOAP
Manufacturer: Topco Associates LLC
Category: otc | Type: HUMAN OTC DRUG LABEL
Date: 20100726

ACTIVE INGREDIENTS: TRICLOSAN 0.4600 mL/100.0000 mL

Drug Facts Box - Back Label

Active Ingredient

Triclosan 0.46%

Purpose

Antibacterial

Warnings

For external use only.

Stop using this product and ask doctor if

Irritation or redness develops and lasts.

Keep out of reach of children

In case of accidental ingestion, get medical help or contact a Poison Control Center immediately.

Uses

For washing to decrease bacteria on the skin.

Directions

Pump onto dry hands, Work into a lather vigorously and rinse thoroughly.

Inactive Ingredients

Water (Aqua), Sodium Xylene Sulfonate, Dipropylene Glycol, Glycerin, Sodium PCA, Ammonium Lauryl Sulfate, Cocamidopropyl Betaine, Polyquaternium-10, Fragrance (Parfum), Disodium Phosphate, Cetyl Alcohol, Aloe Barbadensis Leaf Juice, Citric Acid, Methylparaben, Propylparaben, Green 3 (CI 42053), Yellow 10 (CI 47005)

PACKAGE FRONT AND BACK LABELS

7.5OZ Front and Back Labels: tc8.jpg